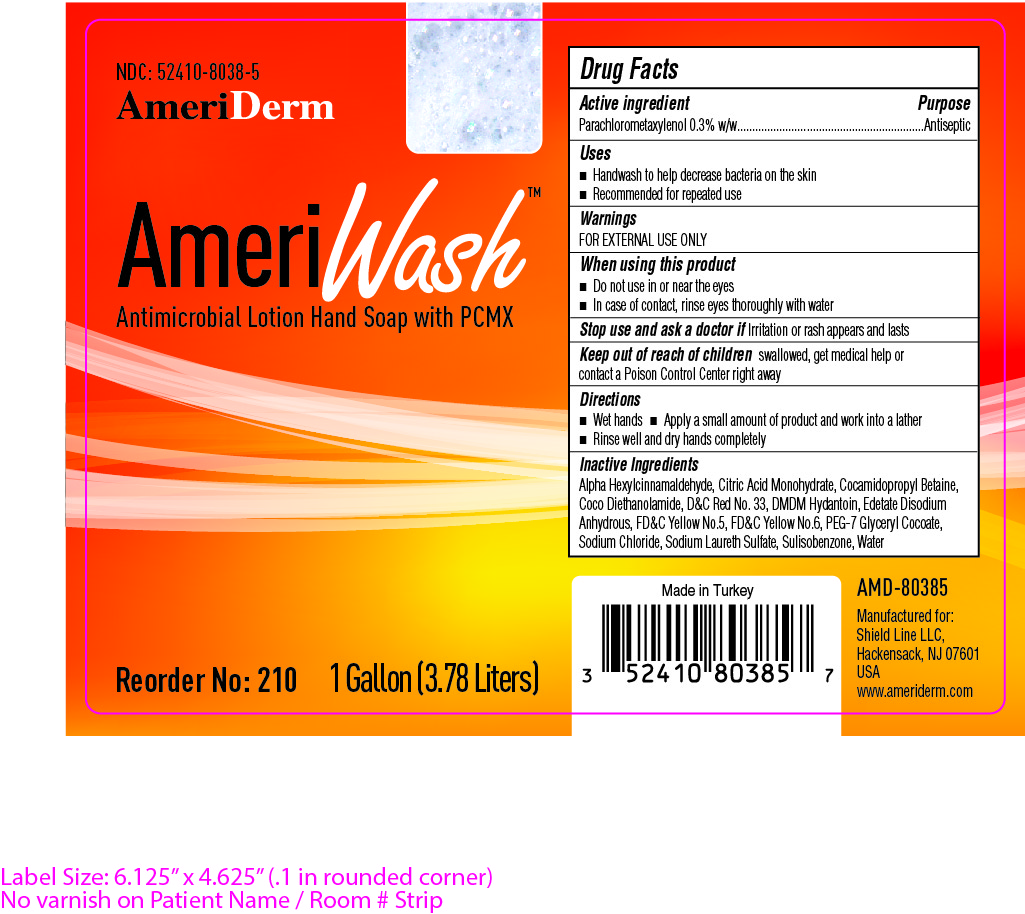 DRUG LABEL: AMERIWASH
NDC: 52410-8038 | Form: LIQUID
Manufacturer: SHIELD LINE LLC
Category: otc | Type: HUMAN OTC DRUG LABEL
Date: 20250815

ACTIVE INGREDIENTS: CHLOROXYLENOL 0.003 mg/1 mL
INACTIVE INGREDIENTS: CITRIC ACID MONOHYDRATE; COCO DIETHANOLAMIDE; DMDM HYDANTOIN; EDETATE DISODIUM ANHYDROUS; FD&C YELLOW NO. 6; FD&C YELLOW NO. 5; SODIUM CHLORIDE; SODIUM LAURETH SULFATE; WATER; D&C RED NO. 33; SULISOBENZONE; COCAMIDOPROPYL BETAINE; PEG-7 GLYCERYL COCOATE; .ALPHA.-HEXYLCINNAMALDEHYDE

AMERIDERM AMERIWASH PCMX 0.3%

Drug Facts Active Ingredient

Parachlorometaxylenol 0.3% w/w

Purpose

Antimicrobial

Uses

- Handwash to help reduce bacteria on the skin that potentially can cause disease
- Recommended for repeat use

Warnings

- FOR EXTERNAL USE ONLY

When using this product

- Do not use in or near the eyes
- Incase of eye contact rinse the eyes thoroughly with water

Stop use and ask a doctor if

- Irritation or rash appears or lasts

Keep out of reach of children

If swallowed, get medical help or contact a Poison Control Center right away

Directions

- Wet hands
- Apply a small amount of product and work into lather
- Rinse well and dry hands completely

Inactive Ingredients

Alpha Hexylcinnamaldehyde, Citric Acid Monohydrate, Cocamidopropyl Betaine, Coco Diethanolamide, D&C Red No. 33, DMDM Hydantoin, Edetate Disodium Anhydrous, FD&C Yellow No.5, FD&C Yellow No.6, PEG-7 Glyceryl Cocoate, Sodium Chloride, Sodium, Laureth Sulfate, Sulisobenzone, Water